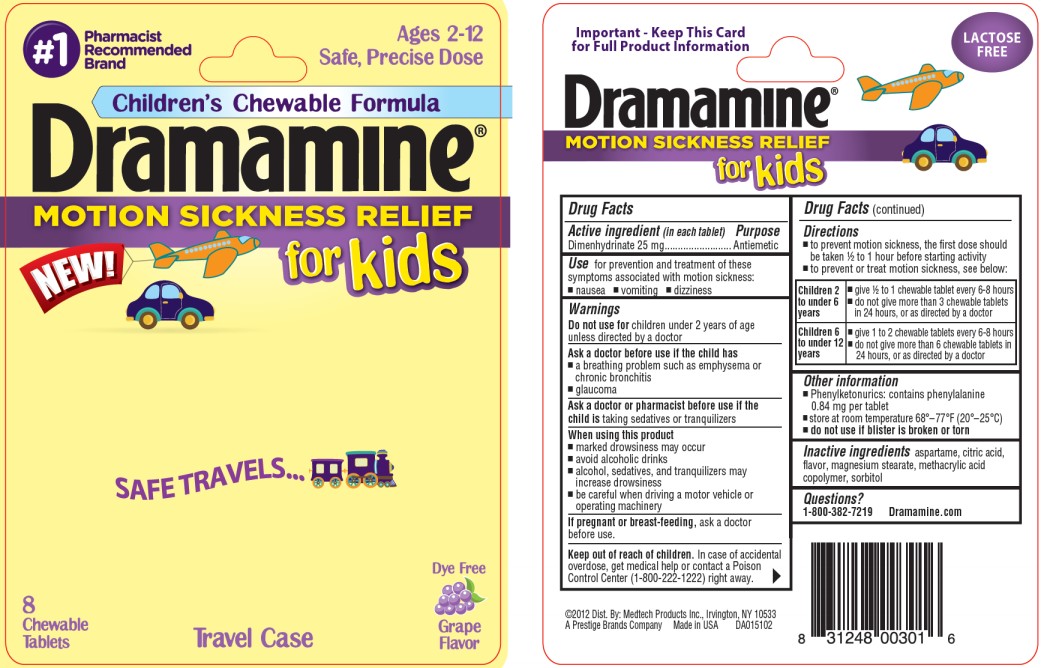 DRUG LABEL: Dramamine for Kids
NDC: 63029-904 | Form: TABLET, CHEWABLE
Manufacturer: Medtech Products Inc.
Category: otc | Type: HUMAN OTC DRUG LABEL
Date: 20250910

ACTIVE INGREDIENTS: DIMENHYDRINATE 25 mg/1 1
INACTIVE INGREDIENTS: ASPARTAME; CITRIC ACID MONOHYDRATE; MAGNESIUM STEARATE; SORBITOL

Dramamine for Kids

Drug Facts

Active ingredient

(in each tablet)

Dimenhydrinate 25 mg

Purpose

Antiemetic

Use

for prevention and treatment of these symptoms associated with motion sickness:

- nausea
- vomiting
- dizziness

Warnings

Do not use for

children under 2 years of age unless directed by a doctor

Ask a doctor before use if the child has

- a breathing problem such as emphysema or chronic bronchitis
- glaucoma

Ask a doctor or pharmacist before use if the child is

taking sedatives or tranquilizers

When using this product

- marked drowsiness may occur
- avoid alcoholic drinks
- alcohol, sedatives, and tranquilizers may increase drowsiness
- be careful when driving a motor vehicle or operating machinery

If pregnant or breast-feeding,

ask a doctor before use.

Keep out of reach of children.

In case of accidental overdose, get medical help or contact a Poison Control Center (1-800-222-1222) right away.

Directions

- to prevent motion sickness, the first dose should be taken ½ to 1 hour before starting activity
- to prevent or treat motion sickness, see below:

Children 2 to under 6 years | - give ½ to 1 chewable tablet every 6-8 hours - do not give more than 3 chewable tablets in 24 hours, or as directed by a doctor
Children 6 to under 12 years | - give 1 to 2 chewable tablets every 6-8 hours - do not give more than 6 chewable tablets in 24 hours, or as directed by a doctor

Other information

- Phenylketonurics: contains phenylalanine 0.84 mg per tablet
- store at room temperature 68º - 77ºF (20º - 25ºC)
- do not use if blister is broken or torn

Inactive ingredients

aspartame, citric acid, flavor, magnesium stearate, methacrylic acid copolymer, sorbitol

Questions?

1-800-382-7219 Dramamine.com

PRINCIPAL DISPLAY PANEL

#1Pharmacist Recommended Brand
Ages 2 – 12
Safe, Precise Dose
Children’s Chewable Formula
Dramamine MOTION SICKNESS RELIEF for Kids
8 Chewable Tablets
Dye Free Grape Flavor